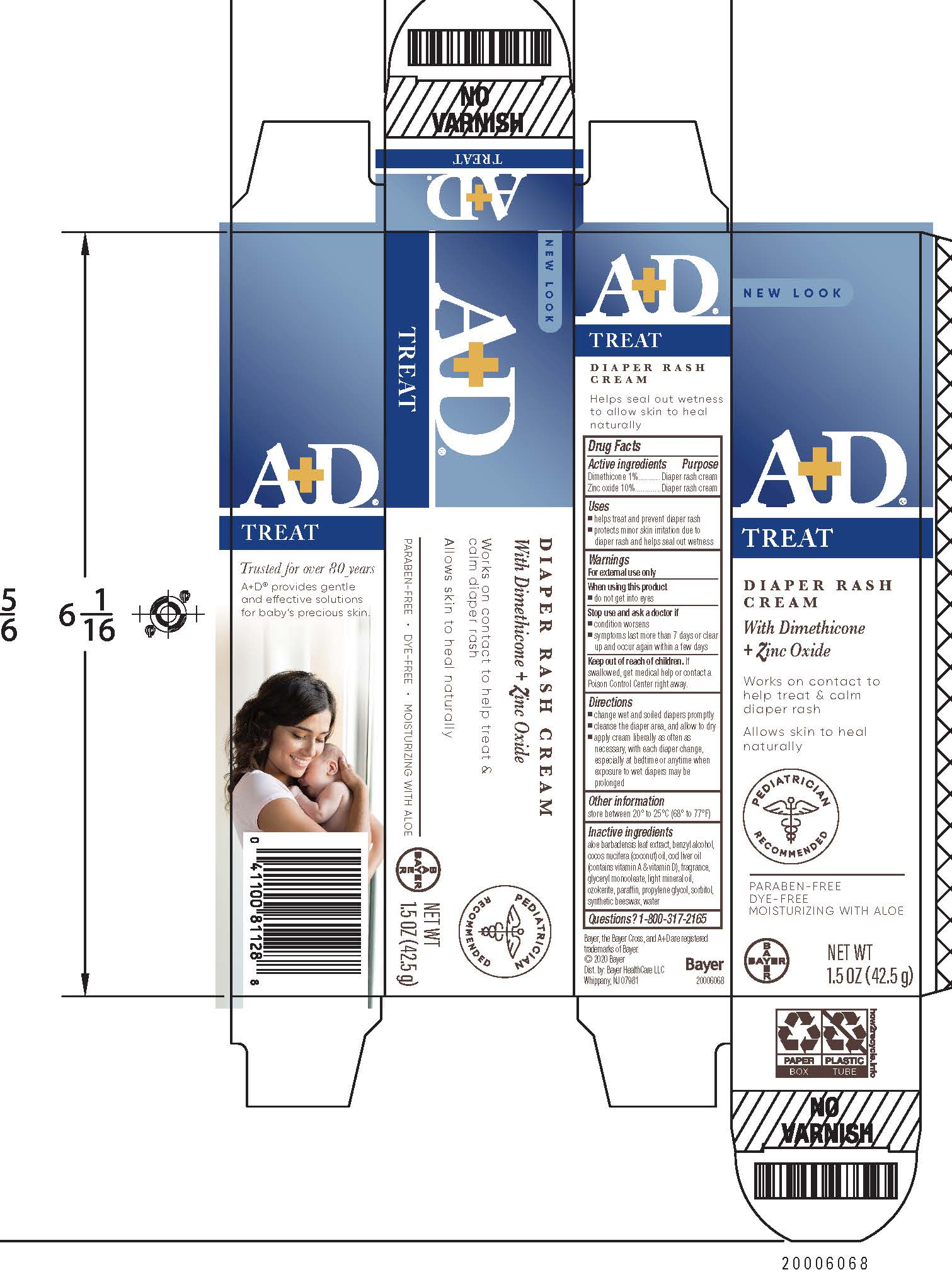 DRUG LABEL: A and D
NDC: 11523-1314 | Form: CREAM
Manufacturer: Bayer HealthCare LLC.
Category: otc | Type: HUMAN OTC DRUG LABEL
Date: 20241206

ACTIVE INGREDIENTS: DIMETHICONE 11.09 mg/1 g; ZINC OXIDE 110.09 mg/1 g
INACTIVE INGREDIENTS: SORBITOL; WATER; ALOE VERA FLOWER; BENZYL ALCOHOL; COCONUT OIL; COD LIVER OIL; LIGHT MINERAL OIL; PARAFFIN; PROPYLENE GLYCOL

A+D
Diaper Rash Cream

ACTIVE INGREDIENT

Dimethicone, Zinc Oxide

Active ingredients | Purpose
Dimethicone 1% | Diaper rash Cream
Zinc Oxide 10% | Diaper rash Cream

Uses

- helps treat and prevent diaper rash
- protects minor skin irritation due to diaper rash and helps seal out wetness

Warnings

For external use only

When using this product

- do not get into eyes

Stop use and ask a doctor if

- condition worsens
- symptoms last more than 7 days or clear up and occur again within a few days

Keep out of reach of children. If swallowed, get medical help or contact a Poison Control Center right away.

Directions

- change wet and soiled diapers promptly
- cleanse the diaper area, and allow to dry
- apply cream liberally as often as necessary, with each diaper change, especially at bedtime or anytime when exposure to wet diapers may be prolonged

Other information

store between 20°C to 25 °C (68° to 77°F)

Inactive Ingredients

Aloe barbadensis extract, benzyl alcohol, coconut oil, cod liver oil (contains vitamin A & Vitamin D), fragrance, glyceryl oleate, light mineral oil, ozokerite, paraffin, propylene glycol, sorbitol, synthetic beeswax, water

PRINCIPAL DISPLAY PANEL - 113g Carton

New Look

A+D®

Treat

Diaper Rash Cream

with Dimethicone and Zinc Oxide

- Works on contact to help treat & calm diaper rash
- Allows skin to heal naturally

PEDIATRICIAN RECOMMENDED

PARABEN-FREE

DYE-FREE

MOISTURIZING WITH ALOE

NET WT

1.5 OZ (42.5 G)